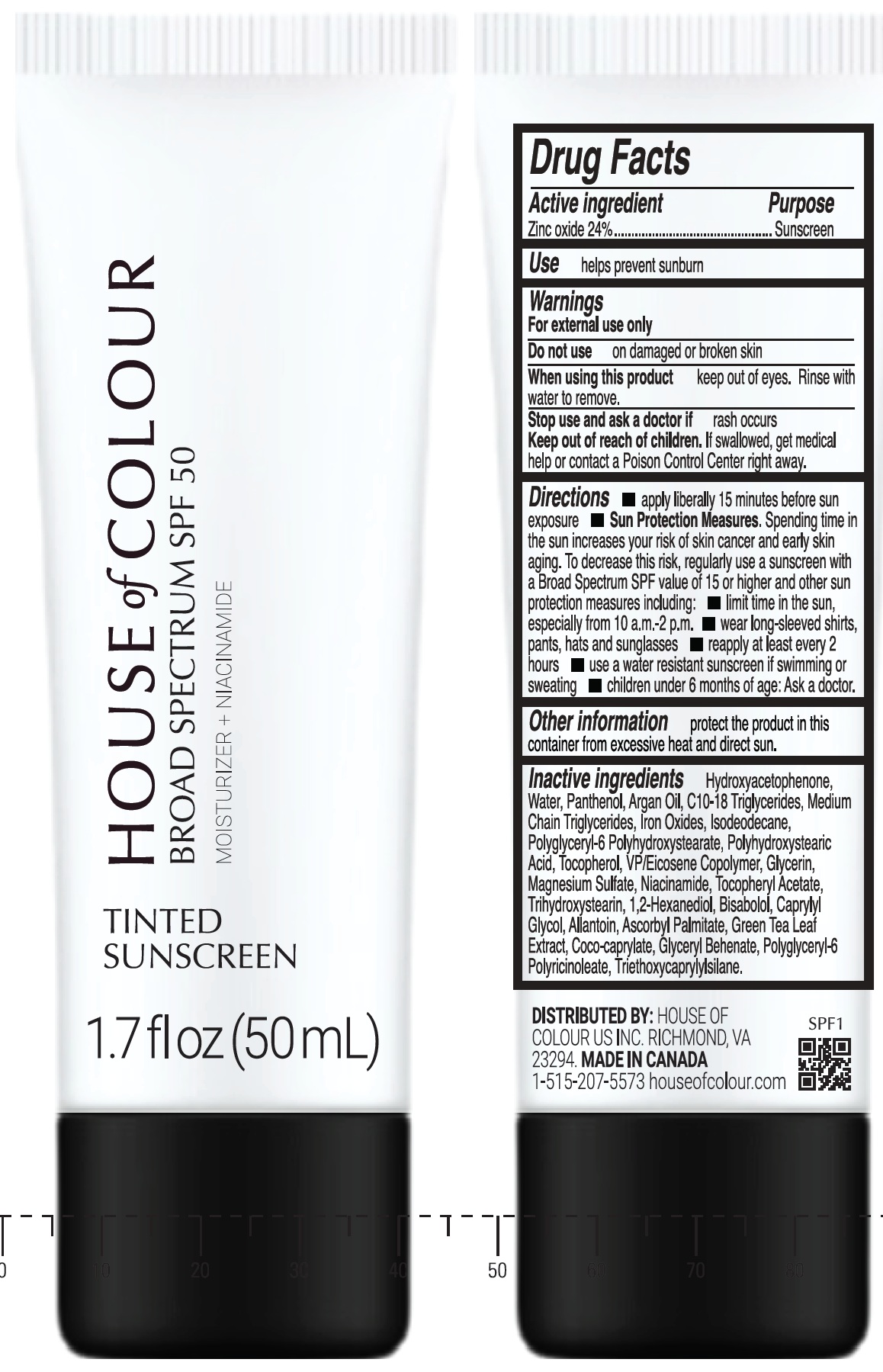 DRUG LABEL: House of Colour Tinted Sunscreen SPF 50
NDC: 85242-000 | Form: CREAM
Manufacturer: House of Colour, Inc.
Category: otc | Type: HUMAN OTC DRUG LABEL
Date: 20260209

ACTIVE INGREDIENTS: ZINC OXIDE 240 mg/1 mL
INACTIVE INGREDIENTS: HYDROXYACETOPHENONE; WATER; PANTHENOL; ARGAN OIL; C10-18 TRIGLYCERIDES; MEDIUM-CHAIN TRIGLYCERIDES; FERRIC OXIDE RED; ISODODECANE; TOCOPHEROL; GLYCERIN; MAGNESIUM SULFATE; NIACINAMIDE; .ALPHA.-TOCOPHEROL ACETATE; TRIHYDROXYSTEARIN; 1,2-HEXANEDIOL; LEVOMENOL; CAPRYLYL GLYCOL; ALLANTOIN; ASCORBYL PALMITATE; GREEN TEA LEAF; COCO-CAPRYLATE; POLYGLYCERYL-6 POLYRICINOLEATE; TRIETHOXYCAPRYLYLSILANE

House of Colour Tinted Sunscreen SPF 50

Active ingredient

Zinc oxide 24%

Purpose

Sunscreen

Use

helps prevent sunburn

Warnings

For external use only

Do not use

on damaged or broken skin

When using this product

keep out of eyes. Rinse with water to remove.

Stop use and ask a doctor if

rash occurs

Keep out of reach of children.

If swallowed, get medical help or contact a Poison Control Center right away.

Directions

- apply liberally 15 minutes before sun exposure
- Sun Protection Measures.Spending time in the sun increases your risk of skin cancer and early skin aging. To decrease this risk, regularly use a sunscreen with a Broad Spectrum SPF value of 15 or higher and other sun protection measures including:
- limit time in the sun, especially from 10 a.m. -2 p.m.
- wear long-sleeved shirts, pants, hats and sunglasses
- reapply at least every 2 hours
- use a water resistant sunscreen if swimming or sweating
- children under 6 months of age: Ask a doctor.

Other information

protect the product in this container from excessive heat and direct sun.

Inactive ingredients

Hydroxyacetophenone, Water, Panthenol, Argan Oil, C10-18 Triglycerides, Medium Chain Triglycerides, Iron Oxides, Isododecane, Polyglyceryl-6 Polyhydroxystearate, Polyhydroxystearic acid, Tocopherol, VP/Eicosene Copolymer, Glycerin, Magnesium Sulfate, Niacinamide, Tocopheryl Acetate, Trihydroxystearin , 1,2-Hexanediol, Bisabolol, Caprylyl Glycol, Allantoin, Ascorbyl Palmitate, Green Tea Leaf Extract, Coco-caprylate, Glyceryl Behenate, Polyglyceryl-6 Polyricinoleate, Triethoxycaprylylsilane.